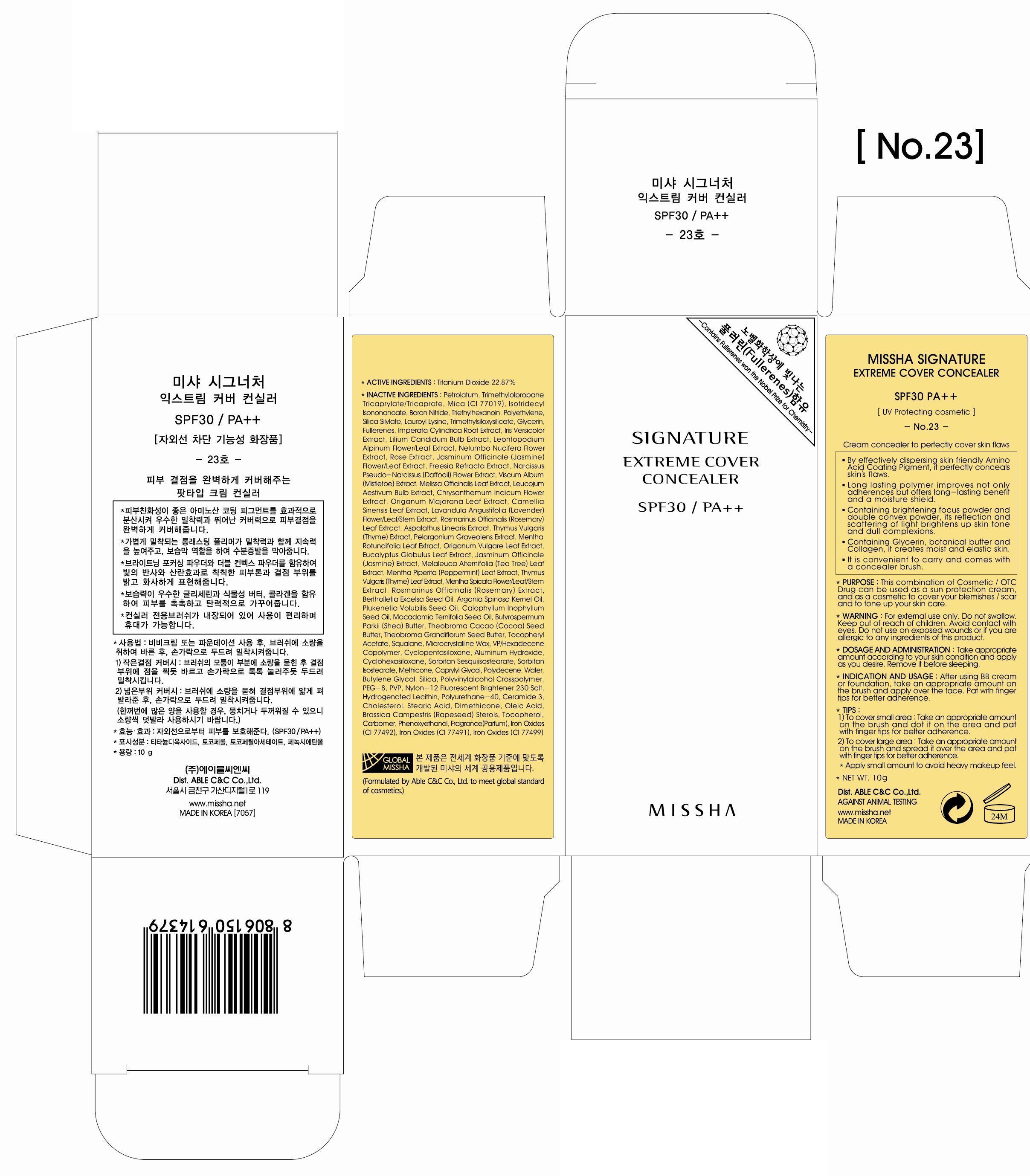 DRUG LABEL: MISSHA SIGNATURE EXTREME COVER CONCEALER
NDC: 13733-018 | Form: CREAM
Manufacturer: ABLE C&C CO., LTD.
Category: otc | Type: HUMAN OTC DRUG LABEL
Date: 20121030

ACTIVE INGREDIENTS: Titanium Dioxide 2.28 g/10 g
INACTIVE INGREDIENTS: Petrolatum; Mica; Isotridecyl Isononanoate; Boron Nitride

ACTIVE INGREDIENT

ACTIVE INGREDIENT: Titanium Dioxide 22.87%

INACTIVE INGREDIENT

INACTIVE INGREDIENTS:
Petrolatum, Trimethylolpropane Tricaprylate/Tricaprate, Mica, Isotridecyl Isononanoate, Boron Nitride, Triethylhexanoin, Polyethylene, Silica Silylate, Lauroyl Lysine, Trimethylsiloxysilicate, Glycerin,Fullerenes, Imperata Cylindrica Root Extract, Iris Versicolor Extract, Lilium Candidum Bulb Extract, Leontopodium Alpinum Flower/Leaf Extract, Nelumbo Nucifera Flower Extract, Rose Extract, Jasminum Officinale (Jasmine) Flower/Leaf Extract, Freesia Refracta Extract, Narcissus Pseudo-Narcissus (Daffodil) Flower Extract, Viscum Album (Mistletoe) Extract, Melissa Officinalis Leaf Extract, Leucojum Aestivum Bulb Extract, Chrysanthemum Indicum Flower Extract, Origanum Majorana Leaf Extract, Camellia Sinensis Leaf Extract, Lavandula Angustifolia (Lavender) Flower/Leaf/Stem Extract, Rosmarinus Officinalis (Rosemary) Leaf Extract, Aspalathus Linearis Extract, Thymus Vulgaris (Thyme) Extract, Pelargonium Graveolens Extract, Mentha Rotundifolia Leaf Extract, Origanum Vulgare Leaf Extract, Eucalyptus Globulus Leaf Extract, Jasminum Officinale (Jasmine) Extract, Melaleuca Alternifolia (Tea Tree) Leaf Extract, Mentha Piperita (Peppermint) Leaf Extract, Thymus Vulgaris (Thyme) Leaf Extract, Mentha Spicata Flower/Leaf/Stem Extract, Rosmarinus Officinalis (Rosemary) Extract, Bertholletia Excelsa Seed Oil, Argania Spinosa Kernel Oil, Plukenetia Volubilis Seed Oil, Calophyllum Inophyllum Seed Oil, Macadamia Ternifolia Seed Oil, Butyrospermum Parkii (Shea) Butter, Theobroma Cacao (Cocoa) Seed Butter, Theobroma Grandiflorum Seed Butter, Tocopheryl Acetate, Squalane, Microcrystalline Wax, VP/Hexadecene Copolymer, Cyclopentasiloxane, Aluminum Hydroxide, Cyclohexasiloxane, Sorbitan Sesquiisostearate, Sorbitan Isostearate, Methicone, Caprylyl Glycol, Polydecene, Water, Butylene Glycol, Silica, Polyvinylalcohol Crosspolymer, PEG-8, PVP, Nylon-12 Fluorescent Brightener 230 Salt, Hydrogenated Lecithin, Polyurethane-40, Ceramide 3, Cholesterol, Stearic Acid, Dimethicone, Oleic Acid, Brassica Campestris (Rapeseed) Sterols, Tocopherol, Carbomer, Phenoxyethanol, Fragrance(Parfum), Iron Oxides

PURPOSE

PURPOSE: This combination of Cosmetic / OTC Drug can be used as a sun protection cream, and as a cosmetic to cover your blemishes / scar and to tone up your skin care.

WARNINGS

WARNING:
For external use only.
Do not swallow.
Keep out of reach of children.
Avoid contact with eyes.
Do not use on exposed wounds or if you are allergic to any ingredients of this product.

KEEP OUT OF REACH OF CHILDREN

INDICATIONS AND USAGE

INDICATION AND USAGE:
After using BB cream or foundation, take an appropriate amount on the brush and apply over the face.
Pat with finger tips for better adherence.

- TIPS :
1) To cover small area: Take an appropriate amount on the brush and dot it on the area and pat with finger tips for better adherence.
2) To cover large area: Take an appropriate amount on the brush and spread it over the area and pat with finger tips for better adherence.

DOSAGE AND ADMINISTRATION

Take appropriate amount according to your skin condition and apply as you desire.
Remove it before sleeping.